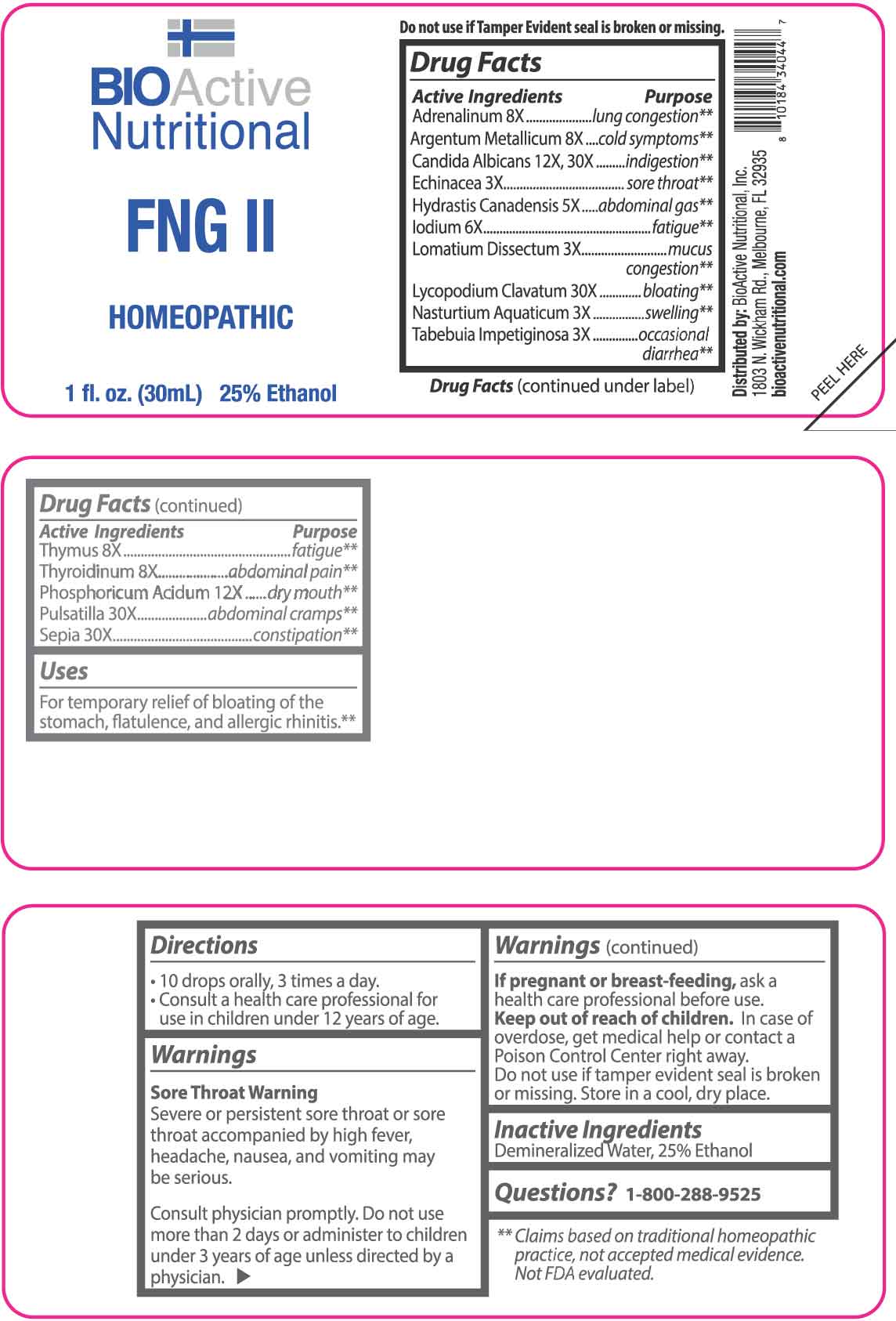 DRUG LABEL: FNG
NDC: 43857-0424 | Form: LIQUID
Manufacturer: BioActive Nutritional, Inc.
Category: homeopathic | Type: HUMAN OTC DRUG LABEL
Date: 20251218

ACTIVE INGREDIENTS: ECHINACEA ANGUSTIFOLIA WHOLE 3 [hp_X]/1 mL; LOMATIUM DISSECTUM ROOT 3 [hp_X]/1 mL; NASTURTIUM OFFICINALE 3 [hp_X]/1 mL; TABEBUIA IMPETIGINOSA BARK 3 [hp_X]/1 mL; GOLDENSEAL 5 [hp_X]/1 mL; IODINE 6 [hp_X]/1 mL; EPINEPHRINE 8 [hp_X]/1 mL; SILVER 8 [hp_X]/1 mL; SUS SCROFA THYMUS 8 [hp_X]/1 mL; THYROID 8 [hp_X]/1 mL; PHOSPHORIC ACID 12 [hp_X]/1 mL; CANDIDA ALBICANS 12 [hp_X]/1 mL; LYCOPODIUM CLAVATUM SPORE 30 [hp_X]/1 mL; PULSATILLA VULGARIS WHOLE 30 [hp_X]/1 mL; SEPIA OFFICINALIS JUICE 30 [hp_X]/1 mL
INACTIVE INGREDIENTS: WATER; ALCOHOL

DRUG FACTS:

ACTIVE INGREDIENTS:

Adrenalinum 8X, Argentum Metallicum 8X, Candida Albicans 12X, 30X, Echinacea 3X, Hydrastis Canadensis 5X, Iodium 6X, Lomatium Dissectum 3X, Lycopodium Clavatum 30X, Nasturtium Aquaticum 3X, Tabebuia Impetiginosa 3X, Thymus 8X, Thyroidinum 8X, Phosphoricum Acidum 12X, Pulsatilla 30X, Sepia 30X.

PURPOSE:

Adrenalinum – lung congestion,** Argentum Metallicum – cold symptoms,** Candida Albicans - indigestion,** Echinacea – sore throat,** Hydrastis Canadensis – abdominal gas,** Iodium - fatigue,** Lomatium Dissectum – mucus congestion,** Lycopodium Clavatum - bloating,** Nasturtium Aquaticum - swelling,** Tabebuia Impetiginosa – occasional diarrhea,** Thymus - fatigue,** Thyroidinum – abdominal pain,** Phosphoricum Acidum – dry mouth,** Pulsatilla – abdominal cramps,** Sepia – constipation**

**Claims based on traditional homeopathic practice, not accepted medical evidence. Not FDA evaluated.

USES:

For temporary relief of bloating of the stomach, flatulence, and allergic rhinitis.**

**Claims based on traditional homeopathic practice, not accepted medical evidence. Not FDA evaluated.

WARNINGS:

Sore Throat Warning

Severe or persistent sore throat or sore throat accompanied by high fever, headache, nausea, and vomiting may be serious.

Consult physician promptly. Do not use more than 2 days or administer to children under 3 years of age unless directed by a physician.

If pregnant or breast-feeding, ask a health care professional before use.

Keep out of reach of children. In case of overdose, get medical help or contact a Poison Control Center right away.

Do not use if tamper evident seal is broken or missing.

Store in a cool, dry place.

KEEP OUT OF REACH OF CHILDREN:

In case of overdose, get medical help or contact a Poison Control Center right away.

DIRECTIONS:

• 10 drops orally, 3 times a day.

• Consult a health care professional for use in children under 12 years of age.

INACTIVE INGREDIENTS:

Demineralized Water, 25% Ethanol

QUESTIONS:

Distributed by:

BioActive Nutritional, Inc.

1803 N. Wickham Rd.

Melbourne, FL 32935

bioactivenutritional.com

1-800-288-9525

PACKAGE LABEL DISPLAY:

BioActive Nutritional

FNG II

HOMEOPATHIC

1 fl. oz. (30 mL)